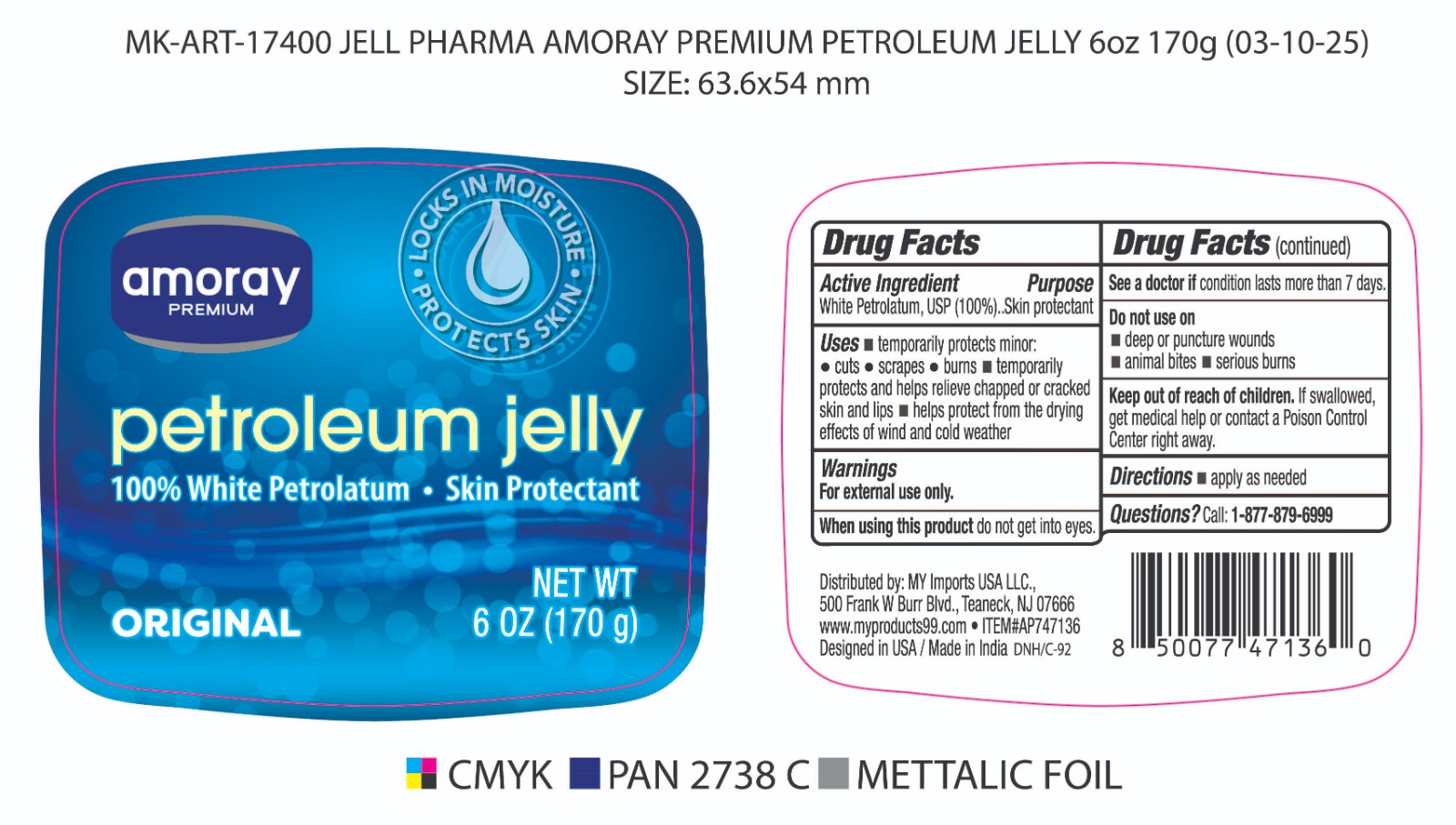 DRUG LABEL: Pure Petrolatum Jelly
NDC: 51628-4600 | Form: JELLY
Manufacturer: MY IMPORTS USA LLC
Category: otc | Type: HUMAN OTC DRUG LABEL
Date: 20260108

ACTIVE INGREDIENTS: PETROLATUM 100 g/100 g
INACTIVE INGREDIENTS: WATER

Amoray Petroleum Jelly

Active Ingredient

White Petrolatum (100% w/w)

Purpose

Skin protectant

Uses

- temporarily protects minor cuts, scrapes, burns and sunburn
- temporarily protects and helps relieve chapped or cracked skin
- helps protect from the drying effects of wind and cold weather
- helps treat and prevent diaper rash
- helps seal out wetness

Warnings:

For external use only

When using this product

- do not get into eyes

Stop use and ask a doctor if

- condition worsens
- symptoms last for more than 7 days or clean up and occur again in a few days

Do not use on

- deep or puncture wounds
- animal bites
- serious burns

Keep out of reach of children

- If swallowed, get medical help or contact a Poison Control Center right away

Directions

- apply as needed

Inactive Ingredient

none